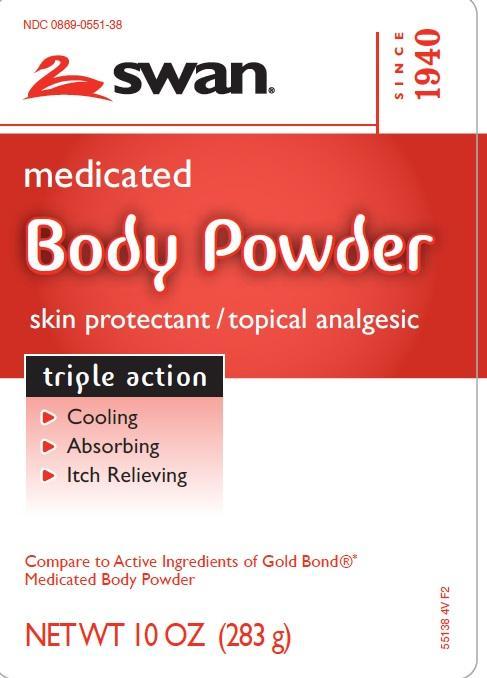 DRUG LABEL: Medicated
NDC: 0869-0551 | Form: POWDER
Manufacturer: Vi-Jon
Category: otc | Type: HUMAN OTC DRUG LABEL
Date: 20130529

ACTIVE INGREDIENTS: MENTHOL 1.5 mg/1 g; ZINC OXIDE 10 mg/1 g
INACTIVE INGREDIENTS: TALC; ACACIA; EUCALYPTOL; METHYL SALICYLATE; SALICYLIC ACID; THYMOL; ZINC STEARATE

Drug Facts

Active Ingredients

Menthol 0.15%

Zinc oxide 1.0%

Purpose

External analgesic

Skin protectant

Uses

Uses for the temporary relief of paina and itching due to:

- monor cuts
- sunburn
- insect bites
- poison ivy
- poison oak
- poison sumac
- scrapes
- minor burns
- minor skin irritations

dries the oozing and weeping of:

- poison ivy
- poison oak
- poison sumac

Warnings

For external use only

When using this product

avoid contact with the eyes

Stop use and ask a doctor if

condition worsens, or if symptoms persist for more than 7 days or clear up and occur again within a few days

Keep out of reach of children

If swallowed, get medical help or contact a Poison Control Center right away

Directions

adults and children 2 years of age and older - apply to affected area not more than 3 to 4 times daily

children under 2 years of age - do not use, consult a doctor

- for best results dry skin thoroughly before applying

Inactive ingredients

talc, acacia, eucalyptol, methyl salicylate, salicylic acid, thymol, zinc stearate

disclaimer

This product is sold by weight, not by volume. Some settling may occur during handling and shipping

Made in the USA with US and foreign components

Adverse Reactions

Vi-Jon

One Swan Drive

Smyrna, TN 37167

Principal Display Panel

NDC 0869-0551-38

SWAN

medicated

Body Powder

skin protectant/topical analgesic

triple action

- Cooling
- Absorbing
- Itch Relieving

Compare to Active Ingredients of Gold Bond Medicated Body Powder

NET WT 10 OZ (283 G)